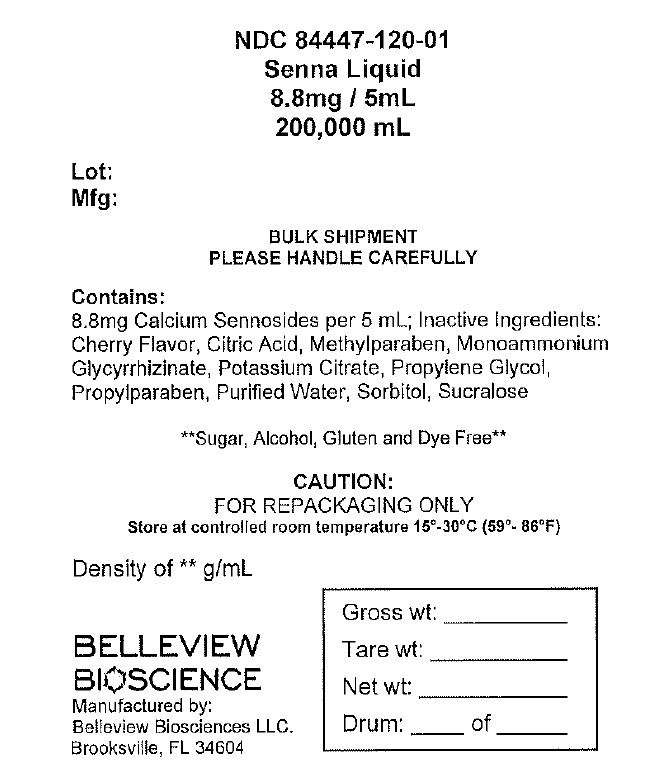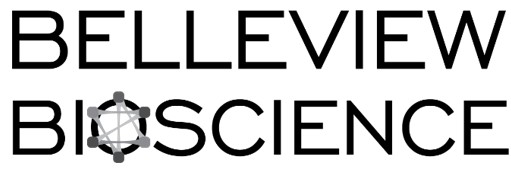 DRUG LABEL: Senna Liquid
NDC: 84447-120 | Form: SYRUP
Manufacturer: Belleview Biosciences
Category: otc | Type: HUMAN OTC DRUG LABEL
Date: 20250523

ACTIVE INGREDIENTS: SENNOSIDES 8.8 mg/5 mL
INACTIVE INGREDIENTS: WATER; SORBITOL; METHYLPARABEN; AMMONIUM GLYCYRRHIZATE; POTASSIUM CITRATE; PROPYLENE GLYCOL; PROPYLPARABEN; CITRIC ACID ACETATE; SUCRALOSE

Senna Liquid, USP 8.8 mg Sennosides per 5 mL

Active Ingredient (per 5 mL)

Sennosides 8.8 mg

Purpose

Laxative

Uses

- relieves occasional constipation (irregularity)
- generally produces bowel movement in 6 to 12 hours

Ask a doctor before use if you have

- stomach pain
- nausea
- vomiting
- noticed a sudden change in bowel habits that has continued for more than 2 weeks

Stop use and ask a doctor if

- you have rectal bleeding or failure to have a bowel movement after use of a laxative. These could be a sign of a serious condition.

If pregnant or breast-feeding,

ask a health professional before use.

Keep out of reach of children.

OVERDOSAGE

In case of overdose, get medical help or contact a Poison Control Center right away.

Directions

- shake well before use
- do not exceed recommended dose

Age | Starting Dose | MMaximum Dose
adults and children; 12 years of age and over | 10 mL to 15 mL once a day preferably at bedtime;; increase as needed or; as recommended by a doctor | 15 mL in the morning and 15 mL at bedtime
children under 12 years of age | ask a doctor | ask a doctor

Other information

- store at 15°C to 30°C (59°F to 86°F). [See USP Controlled Room Temperature]
- protect from light and moisture
- a dark brown, cherry flavored syrup supplied in the following:

NDC 84447-120-01: 200,000 mL Drum

Inactive ingredients

cherry flavor, citric acid, methylparaben, monoammonium glycyrrhizinate, potassium citrate, propylene glycol, propylparaben, purified water, sorbitol, sucralose

Questions or comments?

Call 1-352-549-9917

Manufactured by:
Belleview Biosciences
Brooksville, FL 34604

Do not use

• laxative products for longer than 1 week unless directed by a doctor

BULK SHIPMENT: For institutional or repackaging use only.

NDC 84447-120-01

Senna Liquid

8.8 mg/5 mL

2000, 000 mL

BULK SHIPMENT